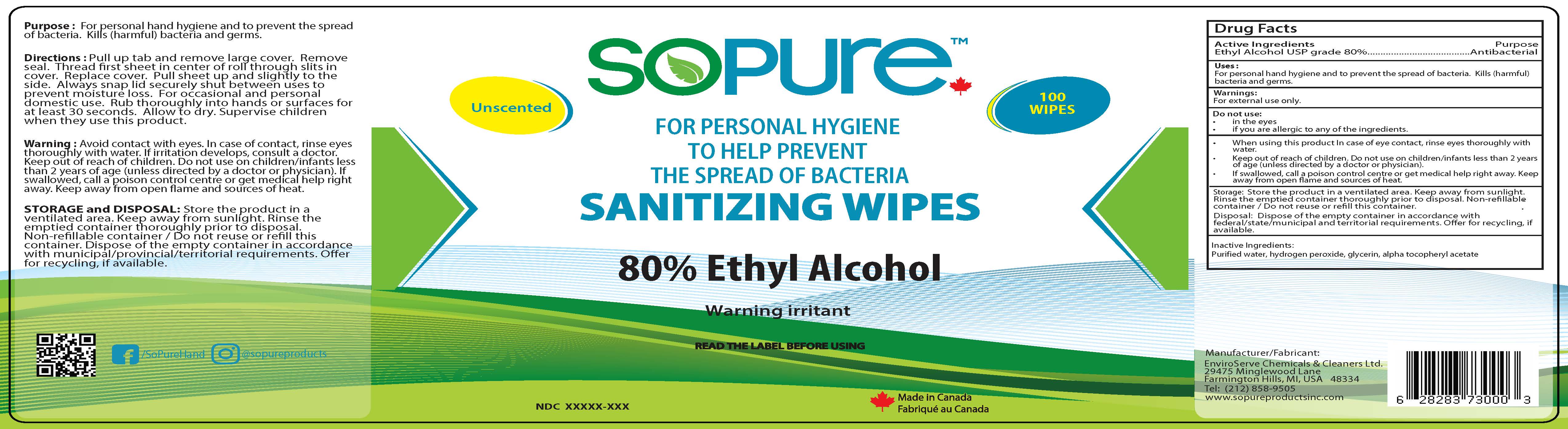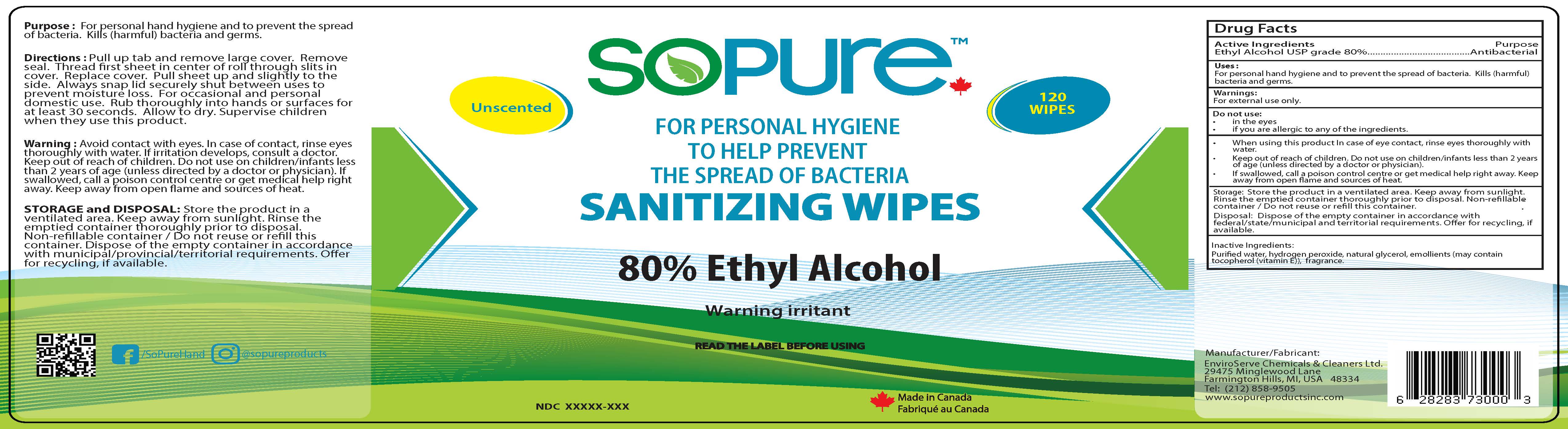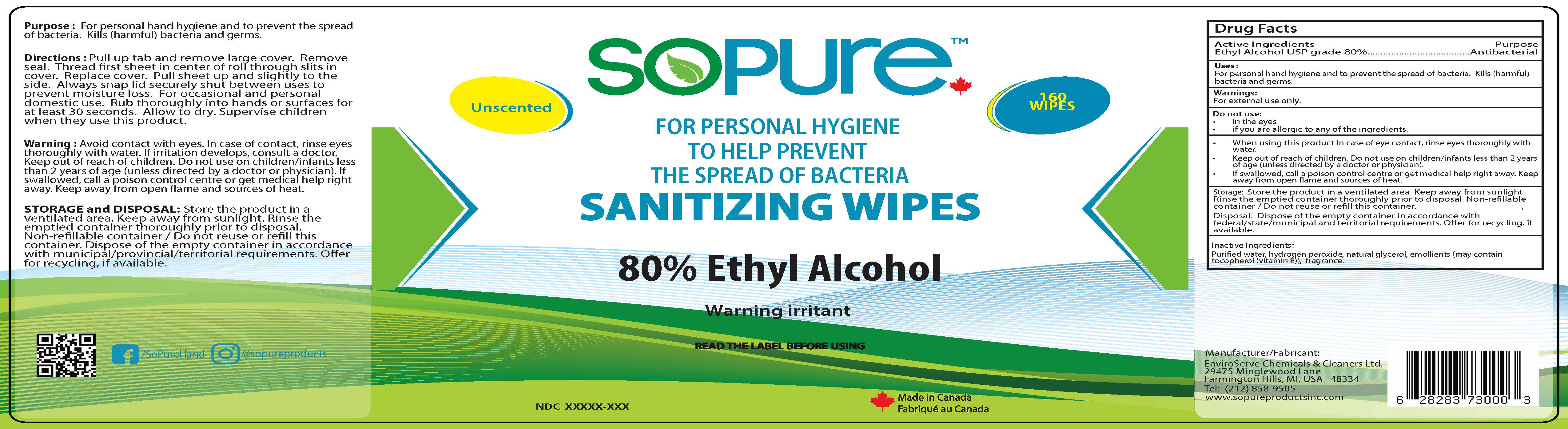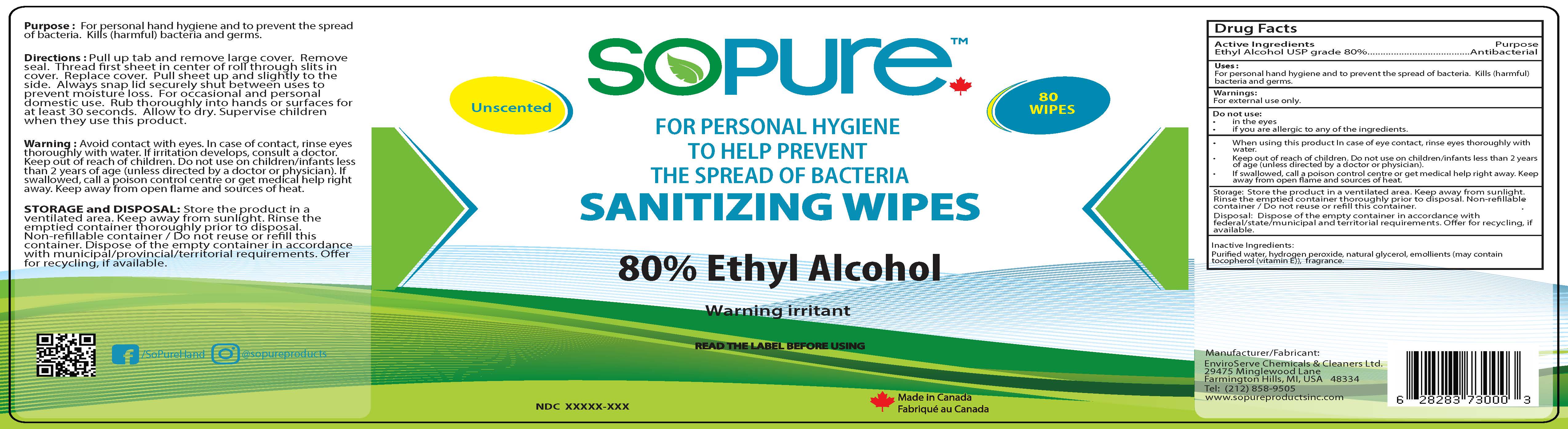 DRUG LABEL: SOPURE
NDC: 80773-002 | Form: CLOTH
Manufacturer: EnviroServe Chemicals & Cleaners Ltd
Category: otc | Type: HUMAN OTC DRUG LABEL
Date: 20211123

ACTIVE INGREDIENTS: ALCOHOL 0.8 1/1 1
INACTIVE INGREDIENTS: WATER; GLYCERIN; .ALPHA.-TOCOPHEROL ACETATE; HYDROGEN PEROXIDE

SOPURE Sanitizing Wipes

Active Ingredient

Ethanol USP 80%v/v

Purpose

Medicated Skin Cleanser Kills harmful bacteria/germs

Warnings

- Avoid contact with eyes. In case of contact, rinse eyes thoroughly with water.
- If irritation develops, consult a doctor. Keep out of reach of children.
- Do not use on children / infants less than 2 years of age (unless directed by a doctor or physician).
- Ifswallowed, call a poison control center or get medical help right away.
- Keep away from open flame and sources of heat.

Uses

Hand Sanitizing wipes Kills harmful bacteria/germs.

Directions

Use as need on basis. Wipe your hands to help prevent spread of bacteria.

Keep out of reach of Children

Do not use on children / infants less than 2 years of age (unless directed by a doctor or physician.)

Inactive Ingredients

Water, glycerin, hydrogen peroxide, alpha tocopherol acetate